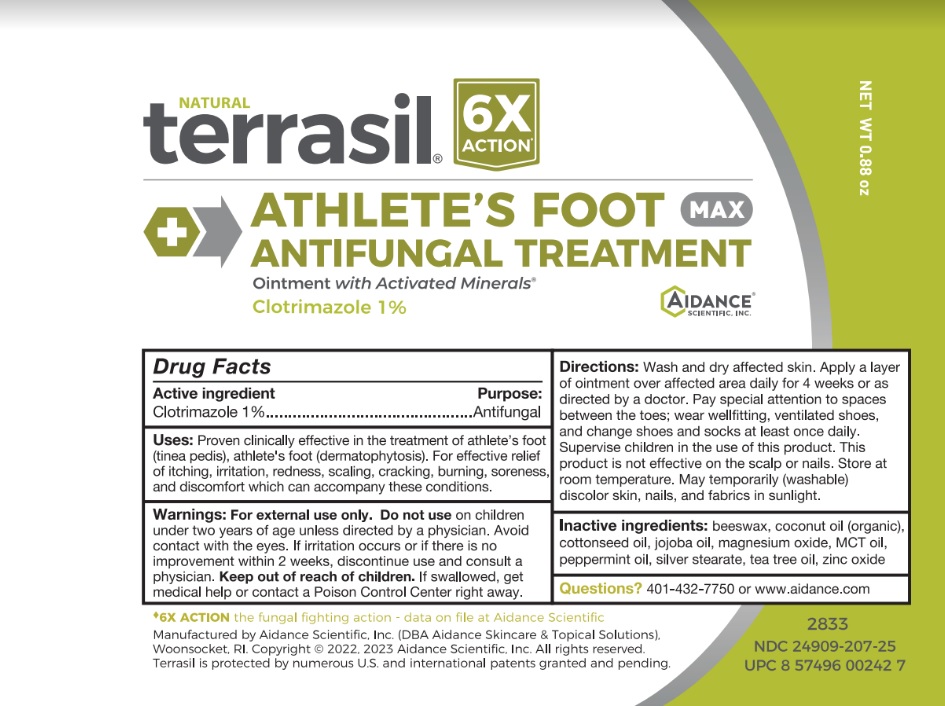 DRUG LABEL: Terrasil Athletes Foot AntiFungal Treatment Max
NDC: 24909-207 | Form: OINTMENT
Manufacturer: Aidance Scientific, Inc., DBA Aidance Skincare & Topical Solutions
Category: otc | Type: HUMAN OTC DRUG LABEL
Date: 20250711

ACTIVE INGREDIENTS: CLOTRIMAZOLE 1 g/100 g
INACTIVE INGREDIENTS: YELLOW WAX; COCONUT OIL; COTTONSEED OIL; JOJOBA OIL; MAGNESIUM OXIDE; PALM OIL; PEPPERMINT OIL; SILVER STEARATE; TEA TREE OIL; ZINC OXIDE

24909-207 terrasil Athlete's Foot Treament Max

Active Ingredient

Clotrimazole 1%

Purpose

Antifungal

Uses

Proven clinically effective in the treatment of athlete’s foot (tinea pedis), athlete's foot (dermatophytosis). For effective relief of itching, irritation, redness, scaling, cracking, burning, soreness, and discomfort which can accompany these conditions.

Warnings

For external use only. Do not use onchildren under two years of age unless directed by a physician. Avoid contact with the eyes. If irritation occurs or if there is no improvement within 2 weeks, discontinue use and consult a physician. Keep out of reach of children.If swallowed, get medical help or contact a Poison Control Center right away.

Directions

Wash and dry affected skin. Apply a layer of ointment over affected area daily for 4 weeks or as directed by a doctor. Pay special attention to spaces between the toes; wear wellfitting, ventilated shoes, and change shoes and socks at least once daily. Supervise children in the use of this product. This product is not effective on the scalp or nails.

Inactive Ingredients

beeswax, coconut oil (organic), cottonseed oil, jojoba oil, magnesium oxide, MCT oil, peppermint oil, silver stearate, tea tree oil, zinc oxide

Other information

Store at room temperature. May temporarily (washable) discolor skin and fabrics in sunlight

Questions?

401-432-7750 or www.aidance.com